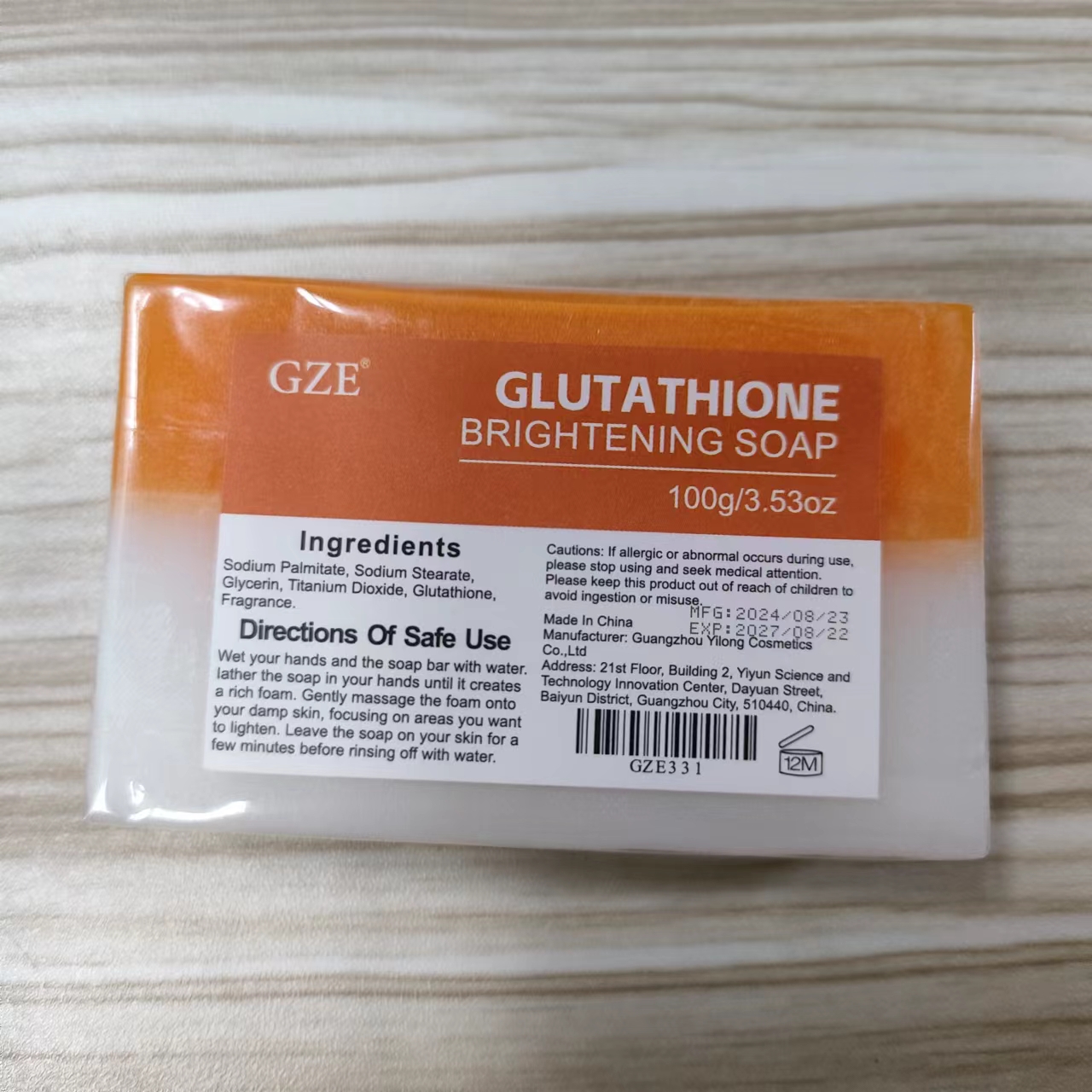 DRUG LABEL: GZE Glutathione BrighteningSoap
NDC: 74458-331 | Form: SOAP
Manufacturer: Guangzhou Yilong Cosmetics Co., Ltd
Category: otc | Type: HUMAN OTC DRUG LABEL
Date: 20241028

ACTIVE INGREDIENTS: GLUTATHIONE 2 g/100 g
INACTIVE INGREDIENTS: SODIUM PALMITATE; SODIUM STEARATE; FRAGRANCE 13576; TITANIUM DIOXIDE; GLYCERIN

GZE GLUTATHIONE BRIGHTENING SOAP

ACTIVE INGREDIENT

Glutathione

INACTIVE INGREDIENT

Sodium Palmitate

Sodium Stearate

Glycerin

Titanium Dioxide

Fragrance

PURPOSE

Brightens skin tone.

INDICATIONS AND USAGE

Wet your hands and the soap bar with water. Iather the soap in your hands until it creates a rich foam. Gently massage the foam onto your damp skin, focusing on areas you want to lighten. Leave the soap on your skin for a few minutes before rinsing off with water.

WARNINGS

For external use only.

Stop use and ask a doctor if rash occurs.

Do not use on damaged or broken skin.

When using this product keep out of eyes. Rinse with water to remove.

Keep out of reach of children. If swallowed, get medical help or contact a Poison Control Center right away.

DOSAGE AND ADMINISTRATION

Wet your hands and the soap bar with water. Iather the soap in your hands until it creates a rich foam. Gently massage the foam onto your damp skin, focusing on areas you want to lighten. Leave the soap on your skin for a few minutes before rinsing off with water.